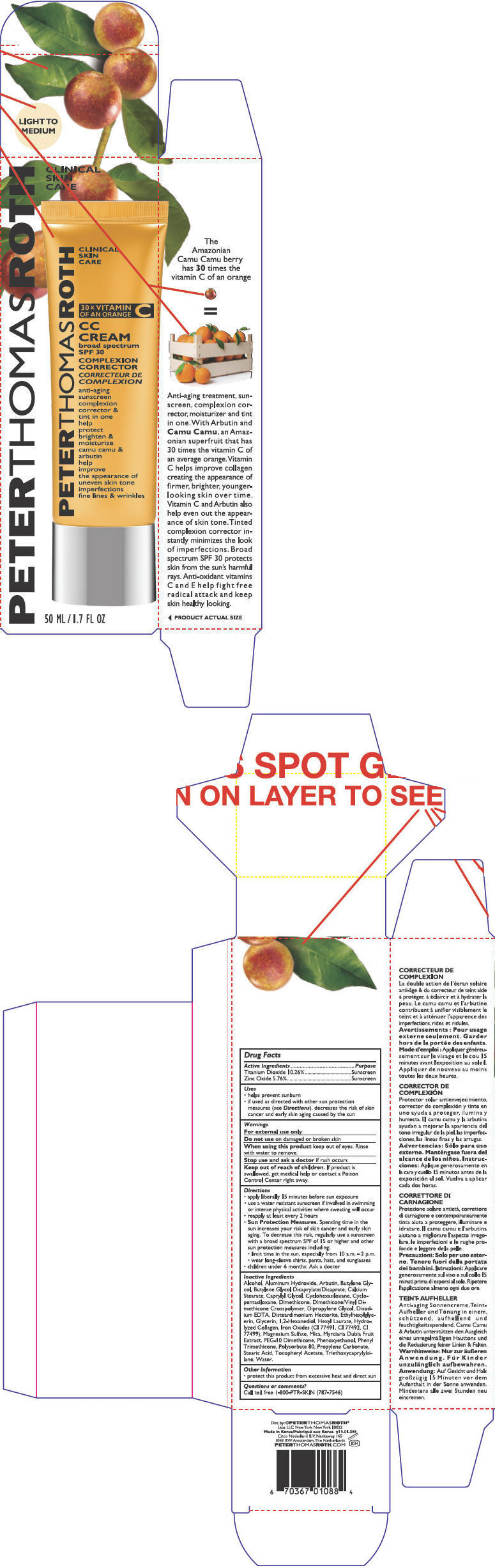 DRUG LABEL: Peter Thomas Roth CC
NDC: 65278-007 | Form: LOTION
Manufacturer: June Jacobs Laboratories LLC
Category: otc | Type: HUMAN OTC DRUG LABEL
Date: 20130130

ACTIVE INGREDIENTS: Titanium Dioxide 102.6 mg/1 mL; Zinc Oxide 57.6 mg/1 mL
INACTIVE INGREDIENTS: Water; Cyclomethicone 5; Glycerin; Phenyl Trimethicone; Dipropylene Glycol; Cyclomethicone 6; Dimethicone; Arbutin; Butylene Glycol Dicaprylate/Dicaprate; Hexyl Laurate; Magnesium Sulfate; Aluminum Hydroxide; Stearic Acid; Polysorbate 80; Caprylyl Glycol; Calcium Stearate; Triethoxycaprylylsilane; Propylene Carbonate; Ethylhexylglycerin; .Alpha.-Tocopherol Acetate; 1,2-Hexanediol; Edetate Disodium; Myrciaria Dubia Fruit; Alcohol; Mica; Butylene Glycol; Phenoxyethanol; Ferric Oxide Red

Peter Thomas Roth CC Cream - Light/Medium

Drug Facts

ACTIVE INGREDIENT

Active Ingredients | Purpose
Titanium Dioxide 10.26% | Sunscreen
Zinc Oxide 5.76% | Sunscreen

Uses

- helps prevent sunburn
- if used as directed with other sun protection measures (see Directions), decreases the risk of skin cancer and early skin aging caused by the sun

Warnings

For external use only

Do not use on damaged or broken skin

When using this product keep out of eyes. Rinse with water to remove.

Stop use and ask a doctor if rash occurs

Keep out of reach of children. If product is swallowed, get medical help or contact a Poison Control Center right away.

Directions

- apply liberally 15 minutes before sun exposure
- use a water resistant sunscreen if involved in swimming or intense physical activities where sweating will occur
- reapply at least every 2 hours
- Sun Protection Measures. Spending time in the sun increases your risk of skin cancer and early skin aging. To decrease this risk, regularly use a sunscreen with a broad spectrum SPF of 15 or higher and other sun protection measures including:
- limit time in the sun, especially from 10 a.m. - 2 p.m.
- wear long-sleeve shirts, pants, hats, and sunglasses
- children under 6 months: Ask a doctor

Inactive Ingredients

Alcohol, Aluminum Hydroxide, Arbutin, Butylene Glycol, Butylene Glycol Dicaprylate/Dicaprate, Calcium Stearate, Caprylyl Glycol, Cyclohexasiloxane, Cyclopentasiloxane, Dimethicone, Dimethicone/Vinyl Dimethicone Crosspolymer, Dipropylene Glycol, Disodium EDTA, Disteardimonium Hectorite, Ethylhexylglycerin, Glycerin, 1,2-Hexanediol, Hexyl Laurate, Hydrolyzed Collagen, Iron Oxides (CI 77491, CI 77492, CI 77499), Magnesium Sulfate, Mica, Myrciaria Dubia Fruit Extract, PEG-10 Dimethicone, Phenoxyethanol, Phenyl Trimethicone, Polysorbate 80, Propylene Carbonate, Stearic Acid, Tocopheryl Acetate, Triethoxycaprylylsilane, Water.

Other Information

- protect this product from excessive heat and direct sun

Questions or comments?

Call toll free 1-800-PTR-SKIN (787-7546)

Dist. by: ©PETERTHOMASROTH® Labs LLC
New York New York 10022

PRINCIPAL DISPLAY PANEL - 50 mL Bottle Label

PETERTHOMASROTH

CLINICAL
SKIN
CARE

30 × VITAMIN
OF AN ORANGE C

CC
CREAM
broad spectrum
SPF 30

COMPLEXION
CORRECTOR

anti-aging
sunscreen
complexion
corrector &
tint in one
help
protect
brighten &
moisturize
camu camu &
arbutin
help
improve
the appearance of
uneven skin tone
imperfections
fine lines & wrinkles

50 ML / 1.7 FL OZ